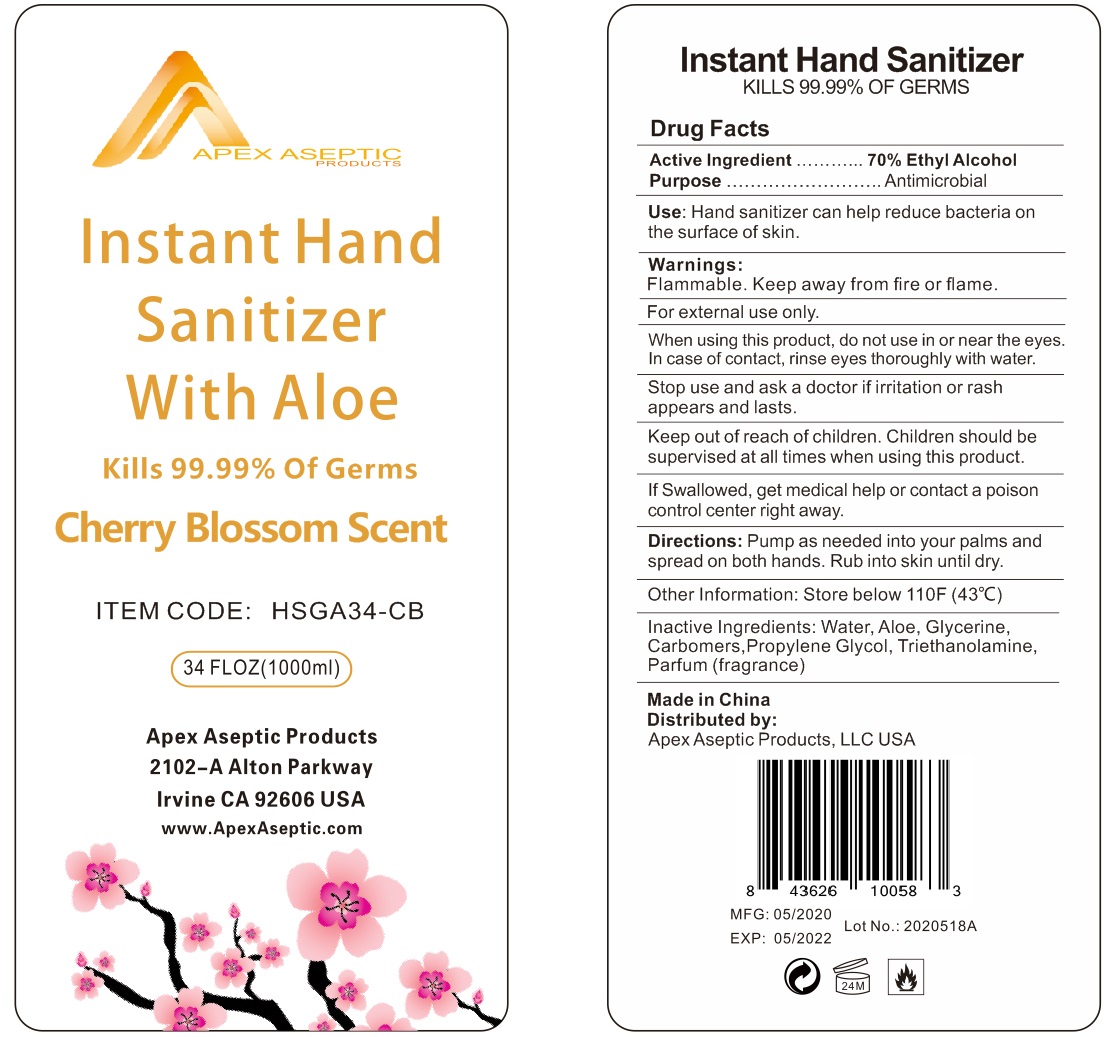 DRUG LABEL: APEX ASEPTIC Instant Hand Sanitizer with Aloe
NDC: 74614-002 | Form: SOLUTION
Manufacturer: TAIZHOU BENGTE FURNITURE CO.,LTD
Category: otc | Type: HUMAN OTC DRUG LABEL
Date: 20200527

ACTIVE INGREDIENTS: ALCOHOL 70 mL/100 mL
INACTIVE INGREDIENTS: WATER; TROLAMINE; GLYCERIN; PROPYLENE GLYCOL

Active ingredient

Ethyl Alcohol 70%

Purpose

Antimicrobial

Use

Hand sanitizer can help reduce bacteria on the surface of skin.

KEEP OUT OF REACH OF CHILDREN

Children should be supervised at all times when using this product.

If swallowed, get medical help or contact a poison control center right away.

warnings:

Flamable, keep away from fire and flame.

For external use only

Do not apply around eyes. Do not use in ears, mouth.

When using this product, do not use in or near the eyes. In case of contact, rinse eyes thoroughlly with water.

Stop use and ask a doctor if irritation or rash appears and lasts.

DOSAGE AND ADMINISTRATION

Pump as needed into your palms and spread on both hands. Rub into skin until dry.

Other Information: Store below 110℉ （43℃）.

Inactive ingredients

Water, Aloe, Glycerin, Carbomer, Propylene Glycol, Triethanolamine, Parfum (Fragrance)